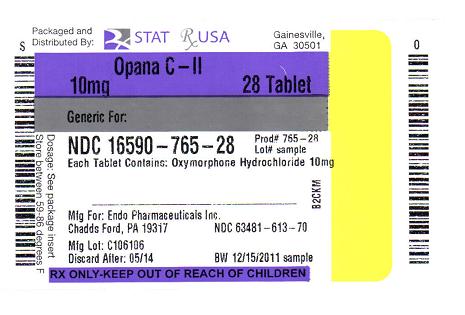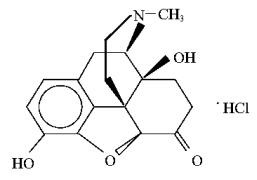 DRUG LABEL: OPANA
NDC: 16590-765 | Form: TABLET
Manufacturer: STAT Rx USA LLC
Category: prescription | Type: HUMAN PRESCRIPTION DRUG LABEL
Date: 20120113
DEA Schedule: CII

ACTIVE INGREDIENTS: OXYMORPHONE HYDROCHLORIDE 10 mg/1 1
INACTIVE INGREDIENTS: LACTOSE MONOHYDRATE; MAGNESIUM STEARATE; STARCH, CORN; D&C RED NO. 30

HIGHLIGHTS OF PRESCRIBING INFORMATION

These highlights do not include all the information needed to use OPANA safely and effectively. See full prescribing information for OPANA.
OPANA (oxymorphone hydrochloride) tablets, CII
Initial U.S. Approval: 1959

1 INDICATIONS AND USAGE

OPANA is an opioid agonist indicated for the relief of moderate to severe acute pain where the use of an opioid is appropriate. (1)

2 DOSAGE AND ADMINISTRATION

- Titrate the dose based on individual response. (2.1)
- OPANA should be taken on an empty stomach, at least one hour prior to or two hours after eating. (2.2)
- Opioid-Naïve Patients: 10 to 20 mg orally every four to six hours. Initiation of therapy with doses higher than 20 mg is not recommended. If necessary, may be initiated with 5 mg (e.g., for renal or hepatic impairment, geriatric patients). (2)
- Conversion to OPANA: Follow recommendations for conversion from other opioids or parenteral oxymorphone. (2.2)
- Cessation of Therapy: Taper gradually. (2.4)

3 DOSAGE FORMS AND STRENGTHS

Tablets: 5 mg and 10 mg. (3)

4 CONTRAINDICATIONS

- Known hypersensitivity to oxymorphone, any other ingredients in OPANA, or morphine analogs (4)
- Respiratory depression in the absence of resuscitative equipment (4)
- Acute or severe bronchial asthma or hypercarbia (4)
- Paralytic ileus (4)
- Moderate or severe hepatic impairment (4)

5 WARNINGS AND PRECAUTIONS

- Respiratory depression: Increased risk in elderly, debilitated patients, and those suffering from conditions accompanied by hypoxia, hypercapnia, or decreased respiratory reserve. (5.1)
- Misuse, abuse, and diversion: OPANA is an opioid agonist and a Schedule II controlled substance with an abuse liability similar to morphine. (5.2)
- CNS effects: Additive CNS-depressive effects when used in conjunction with alcohol, other opioids, or illicit drugs. (5.3)
- Head injury: Effects may be markedly exaggerated. Administer with extreme caution. (5.4)
- Hypotensive effect: Increased risk with compromised ability to maintain blood pressure. Administer with caution to patients in circulatory shock. (5.5)
- Mild hepatic impairment: Use with caution and at lower doses due to higher plasma concentrations than in patients with normal hepatic function (5.6)
- Prolonged gastric obstruction: May occur in patients with gastrointestinal obstruction, especially paralytic ileus. (5.8)
- Sphincter of Oddi: Administer with caution in patients with biliary tract disease. (5.9)
- Impaired mental/physical abilities: Caution must be used with potentially hazardous activities. (5.10)

6 ADVERSE REACTIONS

Adverse reactions (≥ 2% of patients): Nausea, pyrexia, somnolence, vomiting, pruritus, headache, dizziness, constipation, and confusion. (6.1)

To report SUSPECTED ADVERSE REACTIONS, contact Endo Pharmaceuticals Inc. at 1-800-462-3636 or FDA at 1-800-FDA-1088 or www.fda.gov/medwatch.

7 DRUG INTERACTIONS

- CNS depressants: Increased risk of respiratory depression, hypotension, profound sedation, coma or death. When combined therapy with CNS depressant is contemplated, the dose of one or both agents should be reduced. (7.1)
- Mixed agonist/antagonist opioids (i.e., pentazocine, nalbuphine, and butorphanol): May reduce analgesic effect and/or precipitate withdrawal symptoms. (7.2)
- Cimetidine: Combination use may precipitate confusion, disorientation, respiratory depression, apnea, seizures. (7.3)
- Anticholinergics: May result in urinary retention and/or severe constipation, which may lead to paralytic ileus. (7.4)
- Monoamine oxidase inhibitors (MAOIs): Potentiate the action of opioids. OPANA should not be used in patients taking MAOIs or within 14 days of stopping such treatment. (7.5)

8 USE IN SPECIFIC POPULATIONS

- Pregnancy: Based on animal data, may cause fetal harm. (8.1)
- Geriatric patients: OPANA should be used with caution in elderly patients. (8.5)

FULL PRESCRIBING INFORMATION

1 INDICATIONS AND USAGE

OPANA is indicated for the relief of moderate to severe acute pain where the use of an opioid is appropriate.

2 DOSAGE AND ADMINISTRATION

Selection of patients for treatment with OPANA should be governed by the same principles that apply to the use of similar opioid analgesics [see Indications and Usage (1)]. Physicians should individualize treatment in every case [see Dosage and Administration (2.1)], using non-opioid analgesics, opioids on an as needed basis, combination products, and chronic opioid therapy in a progressive plan of pain management such as outlined by the World Health Organization, the Agency for Healthcare Research and Quality, and the American Pain Society.

OPANA should be administered on an empty stomach, at least one hour prior to or two hours after eating [see Clinical Pharmacology (12.3)]

2.1 Individualization of Dosage

As with any opioid drug product, it is necessary to adjust the dosing regimen for each patient individually, taking into account the patient's prior analgesic treatment experience. In the selection of the initial dose of OPANA, attention should be given to the following:

- The total daily dose, potency and specific characteristics of the opioid the patient has been taking previously;
- The relative potency estimate used to calculate the equivalent oxymorphone dose needed;
- The patient’s degree of opioid tolerance;
- The age, general condition, and medical status of the patient;
- Concurrent non-opioid analgesics and other medications;
- The type and severity of the patient's pain;
- The balance between pain control and adverse experiences;
- Risk factors for abuse or addiction, including a prior history of abuse or addiction.

Once therapy is initiated, frequently assess pain relief and other opioid effects. Titrate dose to adequate pain relief (generally mild or no pain). Patients who experience breakthrough pain may require dosage adjustment.

If signs of excessive opioid-related adverse experiences are observed, the next dose may be reduced. Adjust dosing to obtain an appropriate balance between pain relief and opioid-related adverse experiences. If significant adverse events occur before the therapeutic goal of mild or no pain is achieved, the events should be treated aggressively. Once adverse events are adequately managed, continue upward titration to an acceptable level of pain control.

During periods of changing analgesic requirements, including initial titration, frequent contact is recommended between physician, other members of the healthcare team, the patient, and the caregiver/family. Advise patients and family members of the potential common adverse reactions associated with changing opioid doses.

The dosing recommendations below, therefore, can only be considered as suggested approaches to what is actually a series of clinical decisions over time in the management of the pain of each individual patient.

2.2 Initiation of Therapy

Titrate dose to adequate pain relief (generally mild or no pain).

Opioid-Naïve Patients
Patients who have not been receiving opioid analgesics should be started on OPANA in a dosing range of 10 to 20 mg every four to six hours depending on the initial pain intensity. If deemed necessary to initiate therapy at a lower dose (e.g., for renal or hepatic impairment or for geriatric patients), patients may be started with OPANA 5 mg. The dose should be titrated based upon the individual patient’s response to their initial dose of OPANA. This dose can then be adjusted to an acceptable level of analgesia taking into account the pain intensity and adverse reactions experienced by the patient.

Initiation of therapy with doses higher than 20 mg is not recommended because of potential serious adverse reactions [see Clinical Studies (14.1)].

Conversion from Parenteral Oxymorphone to OPANA
Given OPANA’s absolute oral bioavailability of approximately 10%, patients receiving parenteral oxymorphone may be converted to OPANA by administering 10 times the patient’s total daily parenteral oxymorphone dose as OPANA, in four or six equally divided doses (e.g., [IV dose x 10] divided by 4 or 6). For example, approximately 10 mg of OPANA four times daily may be required to provide pain relief equivalent to a total daily IM dose of 4 mg oxymorphone. Due to patient variability with regard to opioid analgesic response, upon conversion patients should be closely monitored to ensure adequate analgesia and to minimize side effects.

Conversion from Other Oral Opioids to OPANA
For conversion from other opioids to OPANA, physicians and other healthcare professionals are advised to refer to published relative potency information, keeping in mind that conversion ratios are only approximate. In general, it is safest to start OPANA therapy by administering half of the calculated total daily dose of OPANA in 4 to 6 equally divided doses, every 4-6 hours. The initial dose of OPANA can be gradually adjusted until adequate pain relief and acceptable side effects have been achieved.

2.3 Maintenance of Therapy

During therapy, continual re-evaluation of the patient receiving OPANA is important, with special attention to the maintenance of pain control and the relative incidence of side effects associated with therapy. If the level of pain increases, effort should be made to identify the source of increased pain, while adjusting the dose [see Dosage and Administration (2.1)].

2.4 Cessation of Therapy

When the patient no longer requires therapy with OPANA, doses should be tapered gradually to prevent signs and symptoms of withdrawal in the physically dependent patient [see Drug Abuse and Dependence (9.3)].

2.5 Patients with Hepatic Impairment

OPANA is contraindicated in patients with moderate or severe hepatic impairment. Use OPANA with caution in patients with mild hepatic impairment, starting with the lowest dose (e.g., 5 mg) and titrating slowly while carefully monitoring side effects [see Warnings and Precautions (5.6) and Clinical Pharmacology (12.3)].

2.6 Patients with Renal Impairment

There are 57% and 65% increases in oxymorphone bioavailability in patients with moderate and severe renal impairment, respectively; treated with extended-release oxymorphone tablets [see Clinical Pharmacology (12.3)]. Accordingly, OPANA should be administered cautiously and in reduced dosages to patients with creatinine clearance rates less than 50 mL/min.

2.7 Use with Central Nervous System Depressants

OPANA, like all opioid analgesics, should be started at 1/3 to 1/2 of the usual dose in patients who are concurrently receiving other central nervous system (CNS) depressants including sedatives or hypnotics, general anesthetics, phenothiazines, tranquilizers, and alcohol, because respiratory depression, hypotension and profound sedation, coma or death may result [see Warnings and Precautions (5.3) and Drug Interactions (7.1)]. When combined therapy with any of the above medications is considered, the dose of one or both agents should be reduced.

Although no specific interaction between oxymorphone and monoamine oxidase inhibitors has been observed, OPANA is not recommended for use in patients who have received MAO inhibitors within 14 days [see Drug Interactions (7.5)].

2.8 Geriatric Patients

Exercise caution in the selection of the starting dose of OPANA for an elderly patient by starting at the low end of the dosing range (e.g., 5 mg) [see Use in Specific Populations (8.5)].

3 DOSAGE FORMS AND STRENGTHS

The 5 mg dosage form is a blue, round, convex tablet debossed with E612 over 5 on one side and plain on the other.

The 10 mg dosage form is a red, round, convex tablet debossed with E613 over 10 on one side and plain on the other.

4 CONTRAINDICATIONS

- OPANA is contraindicated in patients with a known hypersensitivity to oxymorphone or to any of the other ingredients in OPANA, or with known hypersensitivity to morphine analogs such as codeine.
- OPANA is contraindicated in patients with respiratory depression, except in monitored settings and in the presence of resuscitative equipment.
- OPANA is contraindicated in patients with acute or severe bronchial asthma or hypercarbia.
- OPANA is contraindicated in any patient who has or is suspected of having paralytic ileus [see Warning and Precautions (5.8)].
- OPANA is contraindicated in patients with moderate or severe hepatic impairment [see Warnings and Precautions (5.6)].

5 WARNINGS AND PRECAUTIONS

5.1 Respiratory Depression

Respiratory depression is the chief hazard of OPANA. Respiratory depression may occur more frequently in elderly or debilitated patients as well as in those suffering from conditions accompanied by hypoxia or hypercapnia, when even moderate therapeutic doses may dangerously decrease pulmonary ventilation.

Administer OPANA with extreme caution to patients with conditions accompanied by hypoxia, hypercapnia, or decreased respiratory reserve such as: asthma, chronic obstructive pulmonary disease or cor pulmonale, severe obesity, sleep apnea syndrome, myxedema, kyphoscoliosis, CNS depression, or coma. In these patients, even usual therapeutic doses of oxymorphone may decrease respiratory drive while simultaneously increasing airway resistance to the point of apnea. Consider alternative non-opioid analgesics and use OPANA only under careful medical supervision at the lowest effective dose in such patients.

5.2 Misuse, Abuse, and Diversion of Opioids

OPANA contains oxymorphone, a mu opioid agonist and a Schedule II controlled substance with an abuse liability similar to morphine. Opioid agonists are sought by drug abusers and people with addiction disorders and are subject to criminal diversion.

Oxymorphone can be abused in a manner similar to other opioid agonists, legal or illicit. This issue should be considered when prescribing or dispensing oxymorphone in situations where the physician or pharmacist is concerned about an increased risk of misuse, abuse, or diversion.

OPANA tablets may be abused by crushing, chewing, snorting, or injecting the product. These practices pose a significant risk to the abuser that could result in overdose and death [see Drug Abuse and Dependence (9)].

OPANA may be targeted for theft and diversion. Healthcare professionals should contact their State Medical Board, State Board of Pharmacy, or State Control Board for information on how to detect or prevent diversion of this product, and security requirements for storing and handling of OPANA.

Healthcare professionals should advise patients to store OPANA in a secure place, preferably locked and out of the reach of children and other non-caregivers.

Concerns about abuse, misuse, diversion and addiction should not prevent the proper management of pain.

5.3 Additive CNS Depressant Effects

The concomitant use of other CNS depressants including other opioids, general anesthetics, phenothiazines, other tranquilizers, sedatives, hypnotics, and alcohol with oxymorphone may produce increased depressant effects including hypoventilation, hypotension, profound sedation, coma and death [see Drug Interactions (7.1)].

5.4 Use in Patients with Head Injury and Increased Intracranial Pressure

In the presence of head injury, intracranial lesions or a preexisting increase in intracranial pressure, the respiratory depressant effects of opioid analgesics and their potential to elevate cerebrospinal fluid pressure (resulting from vasodilation following CO2 retention) may be markedly exaggerated. Furthermore, opioid analgesics can produce effects on papillary response and consciousness, which may obscure neurologic signs of further increases in intracranial pressure in patients with head injuries.

Administer OPANA with extreme caution in patients who may be particularly susceptible to the intracranial effects of CO2 retention, such as those with evidence of increased intracranial pressure or impaired consciousness. Opioids may obscure the clinical course of a patient with a head injury and should be used only if clinically warranted.

5.5 Hypotensive Effect

OPANA, like all opioid analgesics, may cause severe hypotension in a patient whose ability to maintain blood pressure has been compromised by a depleted blood volume, or after concurrent administration with drugs such as phenothiazines or other agents that compromise vasomotor tone. Administer OPANA with caution to patients in circulatory shock, since vasodilation produced by the drug may further reduce cardiac output and blood pressure.

5.6 Hepatic Impairment

A study of extended-release oxymorphone tablets in patients with hepatic disease indicated greater plasma concentrations than in those with normal hepatic function [see Clinical Pharmacology (12.3)]. Use OPANA with caution in patients with mild impairment, starting with the lowest dose and titrating slowly while carefully monitoring for side effects [see Dosage and Administration (2.2, 2.5)]. OPANA is contraindicated in patients with moderate or severe hepatic impairment.

5.7 Special Risk Groups

Use OPANA with caution in the following conditions: adrenocortical insufficiency (e.g., Addison’s disease), prostatic hypertrophy or urethral stricture, severe impairment of pulmonary or renal function, and toxic psychosis.

Opioids may aggravate convulsions in patients with convulsive disorders, and may induce or aggravate seizures in some clinical settings.

5.8 Gastrointestinal Effects

Opioids diminish propulsive peristaltic waves in the gastrointestinal tract. Monitor for decreased bowel motility in post-operative patients receiving opioids. The administration of OPANA may obscure the diagnosis or clinical course in patients with acute abdominal conditions. OPANA is contraindicated in patients with paralytic ileus.

5.9 Use in Pancreatic/Biliary Tract Disease

OPANA, like other opioids, may cause spasm of the sphincter of Oddi and should be used with caution in patients with biliary tract disease, including acute pancreatitis.

5.10 Driving and Operating Machinery

Opioid analgesics impair the mental and physical abilities needed to perform potentially hazardous activities such as driving a car or operating machinery.

6 ADVERSE REACTIONS

The following serious adverse reactions are discussed elsewhere in the labeling:

- Respiratory depression [see Warnings and Precautions (5.1)]
- Misuse and abuse [see Warnings and Precautions (5.2) and Drug Abuse and Dependence (9)]
- CNS depressant effects [see Warnings and Precautions (5.3)]

Because clinical trials are conducted under widely varying conditions, adverse reaction rates observed in the clinical trials of a drug cannot be directly compared to rates in the clinical trials of another drug and may not reflect the rates observed in clinical practice.

6.1 Clinical Trials Experience

A total of 591 patients were treated with OPANA in controlled clinical trials. The clinical trials consisted of patients with acute post-operative pain (n=557) and cancer pain (n=34) trials.

The following table lists adverse reactions that were reported in at least 2% of patients receiving OPANA in placebo-controlled trials (acute post-operative pain (N=557)).

Table 1: Adverse Reactions Reported in Placebo-Controlled Trials

MedDRA Preferred Term | OPANA (N=557) | Placebo (N=270)
Nausea | 19% | 12%
Pyrexia | 14% | 8%
Somnolence | 9% | 2%
Vomiting | 9% | 7%
Pruritus | 8% | 4%
Headache | 7% | 4%
Dizziness (ExcudingVertigo) | 7% | 2%
Constipation | 4% | 1%
Confusion | 3% | <1%

The common (≥1% - >10%) adverse drug reactions reported at least once by patients treated with OPANA in the clinical trials organized by MedDRA’s (Medical Dictionary for Regulatory Activities) System Organ Class were and not represented in Table 1:
Cardiac disorders: tachycardia
Gastrointestinal disorders: dry mouth, abdominal distention, and flatulence
General disorders and administration site conditions: sweating increased
Nervous system disorders: anxiety and sedation
Respiratory, thoracic and mediastinal disorders: hypoxia
Vascular disorders: hypotension

Other less common adverse reactions known with opioid treatment that were seen <1% in the OPANA trials includes the following:
Abdominal pain, ileus, diarrhea, agitation, disorientation, restlessness, feeling jittery, hypersensitivity, allergic reactions, bradycardia, central nervous system depression, depressed level of consciousness, lethargy, mental impairment, mental status changes, fatigue, depression, clamminess, flushing, hot flashes, dehydration, dermatitis, dyspepsia, dysphoria, edema, euphoric mood, hallucination, hypertension, insomnia, miosis, nervousness, palpitation, postural hypotension, syncope, dyspnea, respiratory depression, respiratory distress, respiratory rate decreased, oxygen saturation decreased, difficult micturition, urinary retention, urticaria, vision blurred, visual disturbances, weakness, appetite decreased, and weight decreased.

6.2 Post-marketing Experience

The following adverse reactions have been identified during post approval use of OPANA. Because these reactions are reported voluntarily from a population of uncertain size, it is not always possible to reliably estimate their frequency or establish a causal relationship to drug exposure.

Nervous system disorder: amnesia, convulsion, memory impairment

7 DRUG INTERACTIONS

7.1 Use with CNS Depressants

The concomitant use of other CNS depressants including sedatives, hypnotics, tranquilizers, general anesthetics, phenothiazines, other opioids, and alcohol may produce additive CNS depressant effects. OPANA, like all opioid analgesics, should be started at 1/3 to 1/2 of the usual dose in patients who are concurrently receiving other central nervous system depressants because respiratory depression, hypotension, and profound sedation, coma and death may result and titrated slowly as necessary for adequate pain relief.

When combined therapy with any of the above medications is considered, the dose of one or both agents should be reduced [see Dosage and Administration (2.7) and Warnings and Precautions (5.3)].

7.2 Interactions with Mixed Agonist/Antagonist Opioid Analgesics

Agonist/antagonist analgesics (i.e., pentazocine, nalbuphine, butorphanol, and buprenorphine) should be administered with caution to a patient who has received or is receiving a course of therapy with a pure opioid agonist analgesic such as oxymorphone. In this situation, mixed agonist/antagonist analgesics may reduce the analgesic effect of oxymorphone and/or may precipitate withdrawal symptoms in these patients.

7.3 Cimetidine

CNS side effects have been reported (e.g., confusion, disorientation, respiratory depression, apnea, seizures) following coadministration of cimetidine with opioid analgesics; a causal relationship has not been established.

7.4 Anticholinergics

Anticholinergics or other medications with anticholinergic activity when used concurrently with opioid analgesics may result in increased risk of urinary retention and/or severe constipation, which may lead to paralytic ileus.

7.5 MAO Inhibitors

Opana is not recommended for use in patients who have received MAO inhibitors within 14 days, because severe and unpredictable potentiation by MAO inhibitors has been reported with opioid analgesics. No specific interaction between oxymorphone and monoamine oxidase inhibitors has been observed, but caution in the use of any opioid in patients taking this class of drugs is appropriate.

8 USE IN SPECIFIC POPULATIONS

8.1 Pregnancy

The safety of using oxymorphone in pregnancy has not been established with regard to possible adverse effects on fetal development. The use of OPANA in pregnancy, in nursing mothers, or in women of child-bearing potential requires that the possible benefits of the drug be weighted against the possible hazards to the mother and the child.

Teratogenic Effects
Pregnancy Category C
There are no adequate and well-controlled studies of oxymorphone in pregnant women. In animal studies, oxymorphone caused decreased fetal and pup weights, an increase in stillbirth, and a decrease in postnatal pup survival at maternal oxymorphone doses equivalent to 0.4 to 4 times the human daily dose of 120 mg (Based on body surface area). OPANA should be used during pregnancy only if the potential benefit justifies the potential risk to the fetus.

In embryo-fetal developmental toxicity studies, pregnant rats and rabbits received oxymorphone hydrochloride at doses up to about 2 times (rats) and 8 times (rabbits) total human daily dose of 120 mg (based on body surface area). No malformations occurred, but reduced fetal weights occurred at maternal doses of 0.8 (rat) and 4 (rabbit) times the total human daily dose of 120 mg (based on body surface area). There were no adverse developmental effects in rats that received 0.4 times or rabbits that received less than 4 times the total human dose. There were no effects of oxymorphone hydrochloride on intrauterine survival at doses in rats ≤2 times, or in rabbits at ≤8 times the human dose (see Non-teratogenic Effects, below). In a study conducted prior to the establishment of Good Laboratory Practices (GLP) and not according to current recommended methodology, a single subcutaneous injection of oxymorphone hydrochloride on gestation day 8 produced malformations in offspring of hamsters that received a dose equivalent to 10 times the total human daily dose of 120 mg (based on body surface area). This dose also produced 83% maternal lethality.

Non-teratogenic Effects
Oxymorphone hydrochloride administration to female rats during gestation in a pre- and postnatal developmental toxicity study reduced mean litter size (18%) at a dose of 25 mg/kg/day, attributed to an increase in the incidence of stillborn pups. An increase in neonatal death occurred at doses ≥5 mg/kg/day (0.4 times a total human daily dose of 120 mg, based on body surface area). Low pup birth weight, decreased post-natal weight gain, and reduced post-natal survival of pups occurred following treatment of the dams with 25 mg/kg/day (about 2 times a total human daily dose of 120 mg, based on body surface area).

Prolonged use of opioid analgesics during pregnancy may cause fetal-neonatal physical dependence. Neonatal withdrawal may occur. Symptoms usually appear during the first days of life and may include convulsions, irritability, excessive crying, tremors, hyperactive reflexes, fever, vomiting, diarrhea, sneezing, yawning, and increased respiratory rate.

8.2 Labor and Delivery

Opioids cross the placenta and may produce respiratory depression in neonates. OPANA is not recommended for use in women during and immediately prior to labor, when use of shorter acting analgesics or other analgesic techniques are more appropriate. Occasionally, opioid analgesics may prolong labor through actions which temporarily reduce the strength, duration, and frequency of uterine contractions. However this effect is not consistent and may be offset by an increased rate of cervical dilatation, which tends to shorten labor. Neonates whose mothers received opioid analgesics during labor should be observed closely for signs of respiratory depression. A specific opioid antagonist, such as naloxone or nalmefene, should be available for reversal of opioid-induced respiratory depression in the neonate.

8.3 Nursing Mothers

It is not known whether oxymorphone is excreted in human milk. Because many drugs, including some opioids, are excreted in human milk, caution should be exercised when OPANA is administered to a nursing woman. Infants exposed to OPANA through breast milk should be monitored for excess sedation and respiratory depression. Withdrawal symptoms can occur in breast-fed infants when maternal administration of an opioid analgesic is stopped, or when breast-feeding is stopped.

8.4 Pediatric Use

Safety and effectiveness of OPANA in pediatric patients below the age of 18 years have not been established.

8.5 Geriatric Use

OPANA should be used with caution in elderly patients [see Clinical Pharmacology (12.3)].

Of the total number of subjects in clinical studies of OPANA, 31% were 65 and over, while 7% were 75 and over. No overall differences in effectiveness were observed between these subjects and younger subjects. There were several adverse events that were more frequently observed in subjects 65 and over compared to younger subjects. These adverse events included dizziness, somnolence, confusion, and nausea. In general, dose selection for elderly patients should be cautious, usually starting at the low end of the dosing range, reflecting the greater frequency of decreased hepatic, renal or cardiac function, and of concomitant disease or other drug therapy

8.6 Hepatic Impairment

In a study of extended-release oxymorphone tablets, patients with mild hepatic impairment were shown to have an increase in bioavailability of 1.6 fold. OPANA should be used with caution in patients with mild impairment. These patients should be started with the lowest dose and titrated slowly while carefully monitoring for side effects. OPANA is contraindicated for patients with moderate and severe hepatic impairment [see Contraindications (4), Warnings and Precautions (5.6), and Dosage and Administration (2.5)].

8.7 Renal Impairment

In a study of extended-release oxymorphone tablets, patients with moderate to severe renal impairment were shown to have an increase in bioavailability ranging from 57-65% [see Clinical Pharmacology (12.3)]. Such patients should be started cautiously with lower doses of OPANA and titrated slowly while monitoring for side effects [see Dosage and Administration (2.6)].

9 DRUG ABUSE AND DEPENDENCE

9.1 Controlled Substance

OPANA contains oxymorphone, a mu opioid agonist and a Schedule II controlled substance with an abuse liability similar to morphine and other opioids. Oxymorphone can be abused and is subject to criminal diversion [see Warnings and Precautions (5.2)].

9.2 Abuse

All patients treated with opioids require careful monitoring for signs of abuse and addiction, since use of opioid analgesic products carries the risk of addiction even under appropriate medical use. Addiction is a primary, chronic, neurobiologic disease, with genetic, psychosocial, and environmental factors influencing its development and manifestations. Addiction is characterized by one or more of the following: impaired control over drug use, compulsive use, use for non-medical purposes, and continued use despite harm. Drug addiction is a treatable disease, utilizing a multidisciplinary approach, but relapse is common.

“Drug-seeking” behavior is very common to addicts and drug abusers. Drug-seeking tactics include emergency calls or visits near the end of office hours, refusal to undergo appropriate examination, testing or referral, repeated claims of loss of prescriptions, tampering with prescriptions, and reluctance to provide prior medical records or contact information for other treating physician(s). “Doctor shopping” (visiting multiple prescribers) to obtain additional prescriptions is common among drug abusers and people suffering from untreated addiction. Preoccupation with achieving adequate pain relief can be appropriate behavior in a patient with poor pain control.

Abuse and addiction are separate and distinct from physical dependence and tolerance. Physicians should be aware that addiction may not be accompanied by concurrent tolerance and symptoms of physical dependence in all addicts. In addition, abuse of opioids can occur in the absence of true addiction and is characterized by misuse for non-medical purposes, often in combination with other psychoactive substances. OPANA, like other opioids, may be diverted for non-medical use. Careful record-keeping of prescribing information, including quantity, frequency, and renewal requests is strongly advised.

OPANA is intended for oral use only. Abuse of OPANA poses a risk of overdose and death. This risk is increased with concurrent abuse of OPANA with alcohol and other substances. Parenteral drug abuse is commonly associated with transmission of infectious diseases such as hepatitis and HIV.

Proper assessment of the patient, proper prescribing practices, periodic re-evaluation of therapy, and proper dispensing and storage are appropriate measures that help to limit abuse of opioid drugs.

9.3 Dependence

Opioid analgesics may cause physical dependence. Physical dependence results in withdrawal symptoms after abrupt discontinuation of a drug or upon administration of an opioid antagonist or mixed opioid agonist/antagonist agent. Withdrawal also may be precipitated through the administration of drugs with opioid antagonist activity, e.g., naloxone, nalmefene, or mixed agonist/antagonist analgesics (pentazocine, butorphanol, buprenorphine, nalbuphine). Physical dependence may not occur to a clinically significant degree until after several days to weeks of continued opioid usage.

Tolerance is the need for increasing doses of opioids to maintain a defined effect such as analgesia (in the absence of disease progression or other external factors). The development of physical dependence and/or tolerance is not unusual during chronic opioid therapy.

OPANA should not be abruptly discontinued [see Dosage and Administration (2.4)]. If OPANA is abruptly discontinued in a physically-dependent patient, an abstinence syndrome may occur. Some or all of the following can characterize this syndrome: restlessness, lacrimation, rhinorrhea, yawning, perspiration, chills, myalgia, and mydriasis. Other symptoms also may develop, including: irritability, anxiety, backache, joint pain, weakness, abdominal cramps, insomnia, nausea, anorexia, vomiting, diarrhea, or increased blood pressure, respiratory rate, or heart rate.

Infants born to mothers physically dependent on opioids will also be physically dependent and may exhibit respiratory difficulties and withdrawal symptoms [see Use in Specific Populations (8.1, 8.2)].

10 OVERDOSAGE

10.1 Symptoms

Acute overdosage with OPANA is characterized by respiratory depression (a decrease in respiratory rate and/or tidal volume, Cheyne-Stokes respiration, cyanosis), extreme somnolence progressing to stupor or coma, skeletal muscle flaccidity, cold and clammy skin, constricted pupils, and sometimes bradycardia and hypotension. In some cases, apnea, circulatory collapse, cardiac arrest, and death may occur.

OPANA may cause miosis, even in total darkness. Pinpoint pupils are a sign of opioid overdose but are not pathognomonic (e.g., pontine lesions of hemorrhagic or ischemic origin may produce similar findings). Marked mydriasis rather than miosis may be seen with hypoxia in overdose situations [see Clinical Pharmacology (12.2)].

10.2 Treatment

In the treatment of OPANA overdosage, primary attention should be given to the re-establishment of a patent airway and institution of assisted or controlled ventilation. Supportive measures (including oxygen and vasopressors) should be employed in the management of circulatory shock and pulmonary edema accompanying overdose as indicated. Cardiac arrest or arrhythmias may require cardiac massage or defibrillation.

The opioid antagonist naloxone hydrochloride is a specific antidote against respiratory depression that may result from overdosage or unusual sensitivity to opioids including OPANA. Nalmefene is an alternative pure opioid antagonist, which may be administered as a specific antidote to respiratory depression resulting from opioid overdose. Since the duration of action of OPANA may exceed that of the antagonist, keep the patient under continued surveillance and administer repeated doses of the antagonist according to the antagonist labeling as needed to maintain adequate respiration.

In patients receiving OPANA, opioid antagonists should not be administered in the absence of clinically significant respiratory or circulatory depression. Administer opioid antagonists cautiously to persons who are known, or suspected to be, physically dependent on any opioid agonist including OPANA. In such cases, an abrupt or complete reversal of opioid effects may precipitate an acute abstinence syndrome. In an individual physically dependent on opioids, administration of the usual dose of the antagonist will precipitate an acute withdrawal syndrome. The severity of the withdrawal syndrome produced will depend on the degree of physical dependence and the dose of the antagonist administered. If respiratory depression is associated with muscular rigidity, administration of a neuromuscular blocking agent may be necessary to facilitate assisted or controlled ventilation. Muscular rigidity may also respond to opioid antagonist therapy.

11 DESCRIPTION

OPANA (oxymorphone hydrochloride) is a semi-synthetic opioid analgesic supplied in 5 mg and 10 mg tablet strengths for oral administration. The tablet strengths describe the amount of oxymorphone hydrochloride per tablet. The tablets contain the following inactive ingredients: lactose monohydrate, magnesium stearate, and pregelatinized starch. In addition, the 5 mg tablets contain FD&C blue No. 2 aluminum lake. The 10 mg tablets contain D&C red No. 30 aluminum lake.

Chemically, oxymorphone hydrochloride is 4, 5α-epoxy-3, 14-dihydroxy-17-methylmorphinan-6-one hydrochloride, a white or slightly off-white, odorless powder, which is sparingly soluble in alcohol and ether, but freely soluble in water. The molecular weight of oxymorphone hydrochloride is 337.80. The pKa1 and pKa2 of oxymorphone at 37°C are 8.17 and 9.54, respectively. The octanol/aqueous partition coefficient at 37°C and pH 7.4 is 0.98.

The structural formula for oxymorphone hydrochloride is as follows:

12 CLINICAL PHARMACOLOGY

12.1 Mechanism of Action

Oxymorphone, a pure opioid agonist, is relatively selective for the mu receptor, although it can interact with other opioid receptors at higher doses.

The precise mechanism of analgesia, the principal therapeutic action of oxymorphone, is unknown. Specific CNS opiate receptors and endogenous compounds with morphine-like activity have been identified throughout the brain and spinal cord and are likely to play a role in the expression and perception of analgesic effects.

12.2 Pharmacodynamics

Pharmacological effects of opioid agonists include analgesia, anxiolysis, euphoria, feelings of relaxation, respiratory depression, constipation, miosis, and cough suppression. Like all pure opioid agonist analgesics, with increasing doses there is increasing analgesia, unlike with mixed agonist/antagonists or non-opioid analgesics, where there is a limit to the analgesic effect with increasing doses. With pure opioid agonist analgesics, there is no defined maximum dose; the ceiling to analgesic effectiveness is imposed only by side effects, the more serious of which may include somnolence and respiratory depression.

Concentration-Efficacy Relationships
The minimum effective plasma concentration of oxymorphone for analgesia varies widely among patients, especially among patients who have been previously treated with potent agonist opioids. As a result, individually titrate patients to achieve a balance between therapeutic and adverse effects. The minimum effective analgesic concentration of oxymorphone for any individual patient may increase over time due to an increase in pain, progression of disease, development of a new pain syndrome and/or development of analgesic tolerance.

Concentration-Adverse Experience Relationships
There is a general relationship between increasing opioid plasma concentration and increasing frequency of adverse experiences such as nausea, vomiting, CNS effects, and respiratory depression.

As with all opioids, the dose of OPANA must be individualized [see Dosage and Administration (2.2)]. The effective analgesic dose for some patients will be too high to be tolerated by other patients.

Effects on the Central Nervous System (CNS)
The principal therapeutic action of oxymorphone is analgesia. In common with other opioids, oxymorphone causes respiratory depression, in part by a direct effect on the brainstem respiratory centers. The respiratory depression involves a reduction in the responsiveness of the brain stem respiratory centers to both increases in carbon dioxide tension and electrical stimulation. Opioids depress the cough reflex by direct effect on the cough center in the medulla. Antitussive effects may occur with doses lower than those usually required for analgesia. Oxymorphone causes miosis, even in total darkness. Pinpoint pupils are a sign of opioid overdose but are not pathognomonic (e.g., pontine lesions of hemorrhagic or ischemic origin may produce similar findings). Marked mydriasis rather than miosis may be seen with hypoxia in overdose situations [see Overdosage (10.1)]. Other therapeutic effects of oxymorphone include anxiolysis, euphoria and feelings of relaxation.

In addition to analgesia, the widely diverse effects of oxymorphone include drowsiness, changes in mood, decreased gastrointestinal motility, nausea, vomiting, and alterations of the endocrine and autonomic nervous system.

Effects on the Gastrointestinal Tract and on Other Smooth Muscle
Gastric, biliary and pancreatic secretions are decreased by oxymorphone. Oxymorphone causes a reduction in motility and is associated with an increase in tone in the antrum of the stomach and duodenum. Digestion of food in the small intestine is delayed and propulsive contractions are decreased. Propulsive peristaltic waves in the colon are decreased, while tone is increased to the point of spasm. The end result may be constipation. Oxymorphone can cause a marked increase in biliary tract pressure as a result of spasm of the sphincter of Oddi; and transient elevations in serum amylase. Oxymorphone may also cause spasm of the sphincter of the urinary bladder.

Cardiovascular System Effects
Opioids produce peripheral vasodilation which may result in orthostatic hypotension. Release of histamine can occur and may contribute to opioid-induced hypotension. Manifestations of histamine release may include orthostatic hypotension, pruritus, flushing, red eyes, and sweating. Animal studies have shown that oxymorphone has a lower propensity to cause histamine release than other opioids.

Endocrine System Effects
Opioid agonists have been shown to have a variety of effects on the secretion of hormones. Opioids inhibit the secretion of ACTH, cortisol, and luteinizing hormone (LH) in humans. They also stimulate prolactin, growth hormone (GH) secretion, and pancreatic secretion of insulin and glucagon in humans and other species, rats and dogs. Thyroid stimulating hormone (TSH) has been shown to be both inhibited and stimulated by opioids.

Immune System Effects
Opioids have been shown to have a variety of effects on components of the immune system in in vitro and animal models. The clinical significance of these findings is unknown.

12.3 Pharmacokinetics

Absorption
The absolute oral bioavailability of oxymorphone is approximately 10%. Studies in healthy volunteers reveal predictable relationships between OPANA dosage and plasma oxymorphone concentrations.

Steady-state levels were achieved after three days of multiple dose administration. Under both single-dose and steady-state conditions, dose proportionality has been established for 5 mg, 10 mg and 20 mg doses of OPANA, for both peak plasma levels (Cmax) and extent of absorption (AUC) (see Table 2).

Table 2
Mean (±SD) OPANA Pharmacokinetic Parameters

Regimen | Dosage | Cmax (ng/mL) | AUC (ng•hr/mL) | T1/2 (hr)
Single Dose | 5 mg 10 mg 20 mg | 1.10±0.55 1.93±0.75 4.39±1.72 | 4.48±2.07 9.10±3.40 20.07±5.80 | 7.25±4.40 7.78±3.58 9.43±3.36
Multiple Dose a | 5 mg 10 mg 20 mg | 1.73±0.62 3.51±0.91 7.33±2.93 | 4.63±1.49 10.19±3.34 21.10±7.59 | NA NA NA
NA = not applicable
a Results after 5 days of every 6 hours dosing.

Food Effect
After oral dosing with 40 mg of OPANA in healthy volunteers under fasting conditions or with a high-fat meal, the Cmax and AUC were increased by approximately 38% in fed subjects relative to fasted subjects. As a result, OPANA should be dosed at least one hour prior to or two hours after eating [see Dosage and Administration (2)].

Ethanol Effect
The effect of co-ingestion of alcohol with OPANA has not been evaluated. However, an in vivo study was performed to evaluate the effect of alcohol (40%, 20%, 4% and 0%) on the bioavailability of a single dose of 40 mg of extended-release oxymorphone tablets in healthy, fasted volunteers. Following concomitant administration of 240 mL of 40% ethanol the Cmax increased on average by 70% and up to 270% in individual subjects. Following the concomitant administration of 240 mL of 20% ethanol, the Cmax increased on average by 31% and up to 260% in individual subjects. In some individuals there was also a decrease in oxymorphone peak plasma concentrations. No effect on the release of oxymorphone from the extended-release tablet was noted in an in vitro alcohol interaction study. The mechanism of the in vivo interaction is unknown. Therefore, avoid co-administration of oxymorphone and ethanol.

Distribution
Formal studies on the distribution of oxymorphone in various tissues have not been conducted. Oxymorphone is not extensively bound to human plasma proteins; binding is in the range of 10% to 12%.

Metabolism
Oxymorphone is highly metabolized, principally in the liver, and undergoes reduction or conjugation with glucuronic acid to form both active and inactive products. The two major metabolites of oxymorphone are oxymorphone-3-glucuronide and 6-OH-oxymorphone. The mean plasma AUC for oxymorphone-3-glucuronide is approximately 90-fold higher than the parent compound. The pharmacologic activity of the glucuronide metabolite has not been evaluated. 6-OH-oxymorphone has been shown in animal studies to have analgesic bioactivity. The mean plasma 6-OH-oxymorphone AUC is approximately 70% of the oxymorphone AUC following single oral doses but is essentially equivalent to the parent compound at steady-state.

Excretion
Because oxymorphone is extensively metabolized, <1% of the administered dose is excreted unchanged in the urine. On average, 33% to 38% of the administered dose is excreted in the urine as oxymorphone-3-glucuronide and 0.25% to 0.62% is excreted as 6-OH-oxymorphone in subjects with normal hepatic and renal function. In animals given radiolabeled oxymorphone, approximately 90% of the administered radioactivity was recovered within 5 days of dosing. The majority of oxymorphone-derived radioactivity was found in the urine and feces.

Pharmacokinetics in Special Populations
Elderly
The plasma levels of oxymorphone administered as an extended-release tablet were about 40% higher in elderly (≥65 years of age) than in younger subjects [see Use in Specific Populations (8.5)].

Gender
The effect of gender on the pharmacokinetics of OPANA has not been studied. In a study with an extended-release formulation of oxymorphone, there was a consistent tendency for female subjects to have slightly higher AUCss and Cmax values than male subjects. However, gender differences were not observed when AUCss and Cmax were adjusted by body weight.

Hepatic Impairment
The liver plays an important role in the pre-systemic clearance of orally administered oxymorphone. Accordingly, the bioavailability of orally administered oxymorphone may be markedly increased in patients with moderate to severe liver disease. The effect of hepatic impairment on the pharmacokinetics of OPANA has not been studied. However, in a study with an extended-release formulation of oxymorphone, the disposition of oxymorphone was compared in 6 patients with mild, 5 patients with moderate, and one patient with severe hepatic impairment, and 12 subjects with normal hepatic function. The bioavailability of oxymorphone was increased by 1.6-fold in patients with mild hepatic impairment and by 3.7-fold in patients with moderate hepatic impairment. In one patient with severe hepatic impairment, the bioavailability was increased by 12.2-fold. The half-life of oxymorphone was not significantly affected by hepatic impairment.

Renal Impairment
The effect of renal impairment on the pharmacokinetics of OPANA has not been studied. However, in a study with an extended-release formulation of oxymorphone, an increase of 26%, 57%, and 65% in oxymorphone bioavailability was observed in mild (creatinine clearance 51-80 mL/min; n=8), moderate (creatinine clearance 30-50 mL/min; n=8), and severe (creatinine clearance <30 mL/min; n=8) patients, respectively, compared to healthy controls.

Drug-Drug Interactions
In vitro studies revealed little to no biotransformation of oxymorphone to 6-OH-oxymorphone by any of the major cytochrome P450 (CYP P450) isoforms at therapeutically relevant oxymorphone plasma concentrations.

No inhibition of any of the major CYP P450 isoforms was observed when oxymorphone was incubated with human liver microsomes at concentrations of ≤50 µM. An inhibition of CYP 3A4 activity occurred at oxymorphone concentrations ≥150 µM. Therefore, it is not expected that oxymorphone, or its metabolites will act as inhibitors of any of the major CYP P450 enzymes in vivo.

Increases in the activity of the CYP 2C9 and CYP 3A4 isoforms occurred when oxymorphone was incubated with human hepatocytes. However, clinical drug interaction studies with OPANA ER showed no induction of CYP450 3A4 or 2C9 enzyme activity, indicating that no dose adjustment for CYP 3A4- or 2C9-mediated drug-drug interactions is required.

13 NONCLINICAL TOXICOLOGY

13.1 Carcinogenesis, Mutagenesis, Impairment of Fertility

Carcinogenesis
Long-term studies have been completed to evaluate the carcinogenic potential of oxymorphone in both Sprague-Dawley rats and CD-1 mice. Oxymorphone was administered to Sprague-Dawley rats (2.5, 5, and 10 mg/kg/day in males and 5, 10, and 25 mg/kg/day in females) for 2 years by oral gavage. The systemic drug exposure (AUC ng•h/mL) at the 10 mg/kg/day dose in male rats was 0.34-fold and at the 25 mg/kg/day dose in female rats was 1.5-fold the human exposure at a dose of 260 mg/day. No evidence of carcinogenic potential was observed in rats. Oxymorphone was administered to CD-1 mice (10, 25, 75 and 150 mg/kg/day) for 2 years by oral gavage. The systemic drug exposure (AUC ng•h/mL) at the 150 mg/kg/day dose in mice was 14.5-fold (in males) and 17.3-fold (in females) times the human exposure at a dose of 260 mg/day. No evidence of carcinogenic potential was observed in mice.

Mutagenesis
Oxymorphone hydrochloride was not mutagenic when tested in the in vitro bacterial reverse mutation assay (Ames test) at concentrations of ≤5270 µg/plate, or in an in vitro mammalian cell chromosome aberration assay performed with human peripheral blood lymphocytes at concentrations ≤5000 µg/ml with or without metabolic activation. Oxymorphone hydrochloride tested positive in both the rat and mouse in vivo micronucleus assays. An increase in micronucleated polychromatic erythrocytes occurred in mice given doses of ≥250 mg/kg and in rats given doses of 20 and 40 mg/kg. A subsequent study demonstrated that oxymorphone hydrochloride was not aneugenic in mice following administration of up to 500 mg/kg. Additional studies indicate that the increased incidence of micronucleated polychromatic erythrocytes in rats may be secondary to increased body temperature following oxymorphone administration. Doses associated with increased micronucleated polychromatic erythrocytes also produce a marked, rapid increase in body temperature. Pretreatment of animals with sodium salicylate minimized the increase in body temperature and prevented the increase in micronucleated polychromatic erythrocytes after administration of 40 mg/kg oxymorphone.

Impairment of fertility
Oxymorphone did not affect reproductive function or sperm parameters in male rats at any dose tested (≤50 mg/kg/day). In female rats, an increase in the length of the estrus cycle and decrease in the mean number of viable embryos, implantation sites and corpora lutea were observed at doses of oxymorphone ≥10 mg/kg/day. The dose of oxymorphone associated with reproductive findings in female rats is 0.8 times a total human daily dose of 120 mg based on a body surface area. The dose of oxymorphone that produced no adverse effects on reproductive findings in female rats (i.e., NOAEL) is 0.4-times a total human daily dose of 120 mg based on body surface area.

14 CLINICAL STUDIES

The analgesic efficacy of OPANA has been evaluated in acute pain following orthopedic and abdominal surgeries.

14.1 Orthopedic Surgery

Two double-blind, placebo-controlled, dose-ranging studies in patients with acute moderate to severe pain following orthopedic surgery evaluated the doses of OPANA 10 mg and 20 mg, and 30 mg was included in one study. Both studies demonstrated that OPANA 20 mg provided greater analgesia as measured by total pain relief based on a weighted analysis over 8 hours using a 0-4 categorical, compared to placebo. OPANA 10 mg provided greater analgesia as compared to placebo in one of the two studies. There was no evidence of superiority of the 30 mg dose over the 20 mg dose. However, there was a high rate of naloxone use in patients receiving the OPANA 30 mg dose in the post-operative period [see Dosage and Administration (2.2)].

14.2 Abdominal Surgery

In a randomized, double-blind, placebo-controlled, multiple-dose study, the efficacy of OPANA 10 mg and 20 mg was assessed in patients with moderate to severe acute pain following abdominal surgery. In this study, patients were dosed every 4 to 6 hours over a 48-hour treatment period. OPANA 10 and 20 mg provided greater analgesia, as measured by the mean average pain intensity on a 0-100 mm visual analog scale, over 48 hours, compared to placebo [see Dosage and Administration (2.2)].

16 HOW SUPPLIED/STORAGE AND HANDLING

OPANA tablets are supplied as follows:

5 mg Tablet:
Blue, round, convex tablets debossed with E612 over 5 on one side and plain on the other.

Bottles of 100 tablets with child-resistant closure NDC 63481-612-70

Unit-Dose package of 100 tablets (5 blister cards of 20
tablets, not child-resistant, for hospital use only) NDC 63481-612-75

10 mg Tablet:
Red, round, convex tablets debossed with E613 over 10 on one side and plain on the other.

Bottles of 100 tablets with child-resistant closure NDC 63481-613-70

Unit-Dose package of 100 tablets (5 blister cards of 20
tablets, not child-resistant, for hospital use only) NDC 63481-613-75

OPANA may be targeted for theft and diversion. Healthcare professionals should contact their State Medical Board, State Board of Pharmacy, or State Control Board for information on how to detect or prevent diversion of this product, and security requirements for storing and handling of OPANA.

Healthcare professionals should advise patients to store OPANA in a secure place, preferably locked and out of the reach of children and other non-caregivers.

Store at 25°C (77°F); excursions permitted to 15°-30°C (59°-86°F). [See USP Controlled Room Temperature].

Dispense in tight container as defined in the USP, with a child-resistant closure (as required).

Advise patients to dispose of any unused tablets from a prescription by flushing them down the toilet as soon as they are no longer needed [see Patient Counseling Information (17)].

17 PATIENT COUNSELING INFORMATION

- Advise patients that OPANA contains oxymorphone, which is a morphine-like pain reliever, and should be taken only as directed.
- Advise patients that OPANA is a potential drug of abuse. They should protect it from theft, and it should never be given to anyone other than the individual for whom it was prescribed.
- Advise patients to keep OPANA in a secure place out of the reach of children and pets. Accidental consumption especially in children may result in overdose or death. When OPANA is no longer needed, the unused tablets should be destroyed by flushing down the toilet.
- Advise patients to report episodes of breakthrough pain and adverse experiences occurring during therapy to their doctor. Individualization of dosage is essential to make optimal use of this medication.
- Advise patients not to adjust the dose of OPANA without consulting the prescriber.
- Advise patients that OPANA may cause drowsiness, dizziness, or lightheadedness and may impair mental and/or physical abilities required for the performance of potentially hazardous tasks, such as driving a car, operating machinery, etc.
- Advise patients that OPANA will add to the effect of alcohol and other CNS depressants (such as antihistamines, sedatives, hypnotics, tranquilizers, general anesthetics, phenothiazines, other opioids, and monoamine oxidase [MAO] inhibitors).
- Advise patients not to combine OPANA with alcohol or other central nervous system depressants (sleep aids, tranquilizers) except by the orders of the prescribing physician, because dangerous additive effects may occur, resulting in serious injury or death.
- Advise patients of the potential for severe constipation. Appropriate laxatives and/or stool softeners and other therapeutic approaches should be considered for use with the initiation of OPANA therapy.
- Advise women of childbearing potential who become or are planning to become pregnant to consult their physician regarding the effects of opioid analgesics and other drug use during pregnancy on themselves and their unborn child.
- Advise women of childbearing potential who become or are planning to become pregnant that safe use in pregnancy has not been established. Prolonged use of opioid analgesics during pregnancy may cause fetal-neonatal physical dependence, and neonatal withdrawal may occur.
- Advise patients that if they have been receiving treatment with OPANA for more than a few weeks and cessation of therapy is indicated, it may be appropriate to taper the OPANA dose, rather than abruptly discontinue it, due to the risk of precipitating withdrawal symptoms. Their physician can provide a dose schedule to accomplish a gradual discontinuation of the medication.

Manufactured for:
Endo Pharmaceuticals Inc., Chadds Ford, PA 19317

Manufactured by:
Novartis Consumer Health Inc., Lincoln, NE 68517

2007951 / August 2011